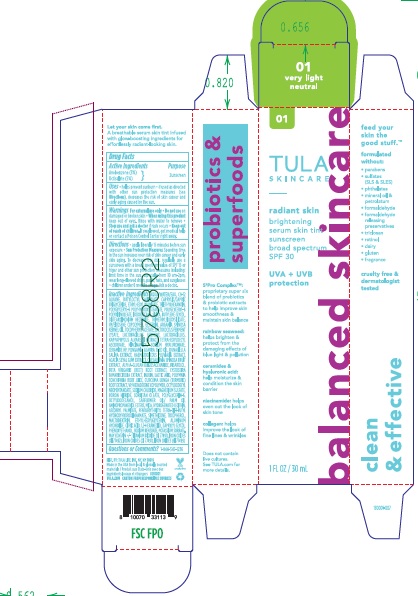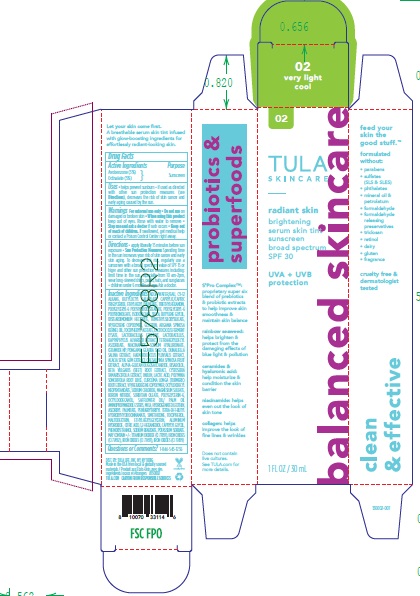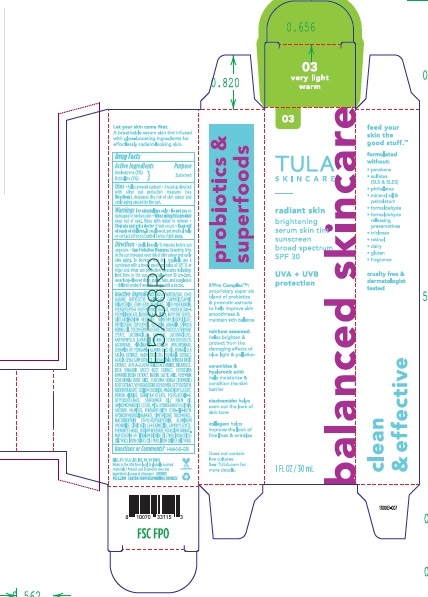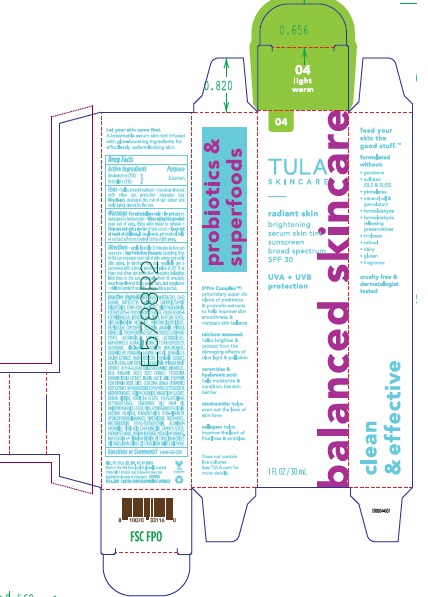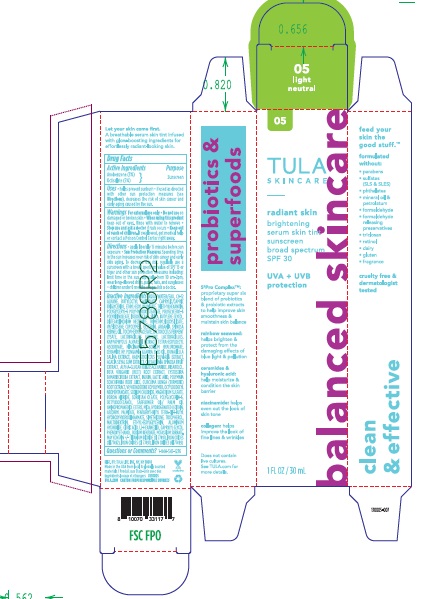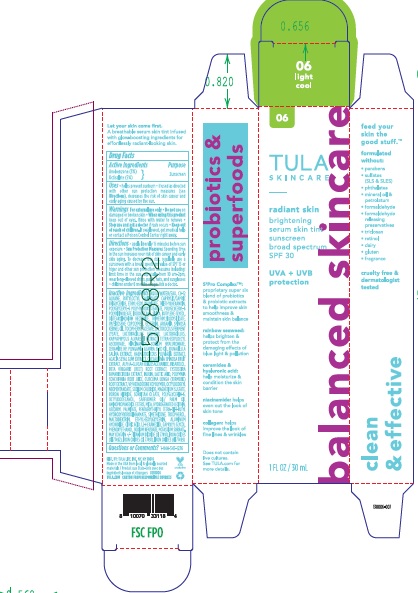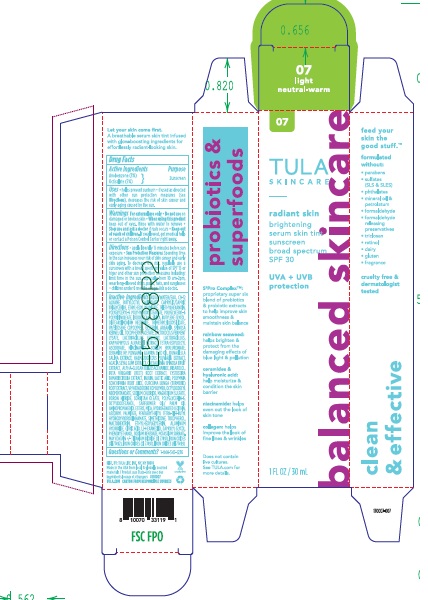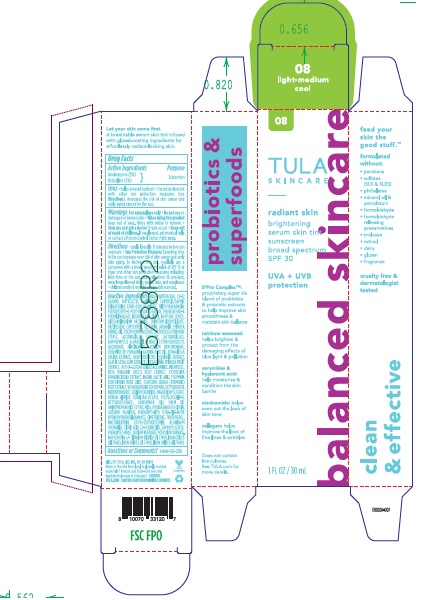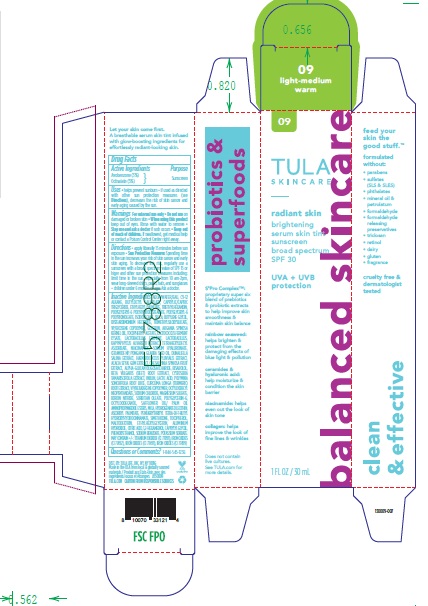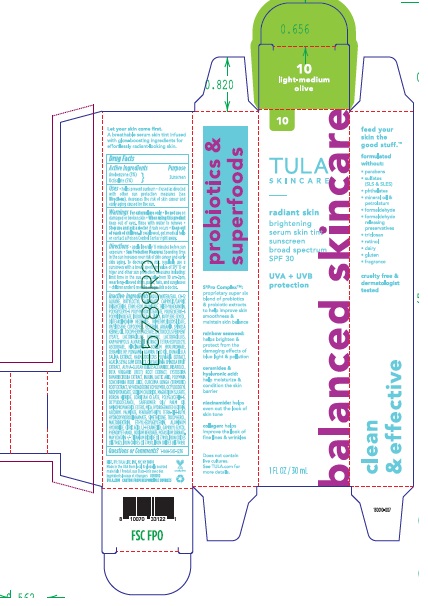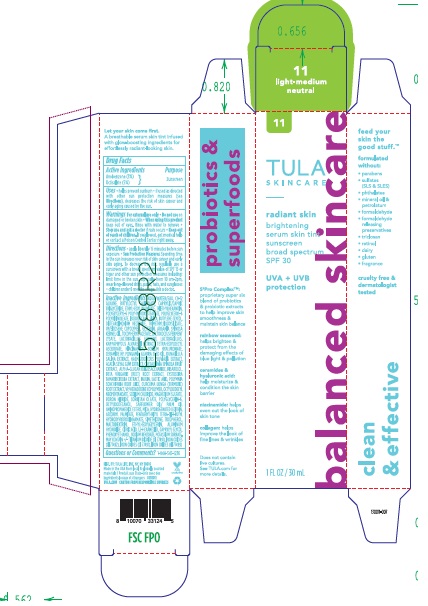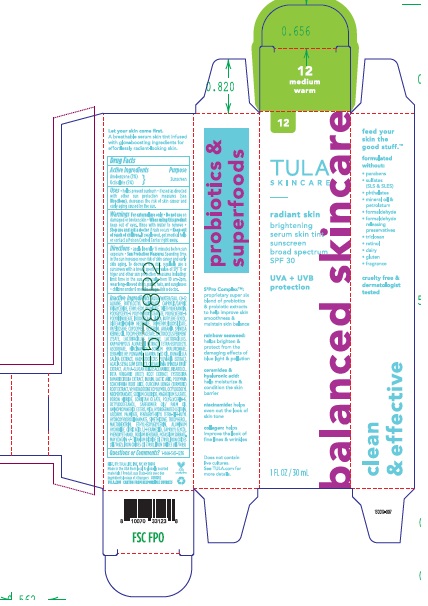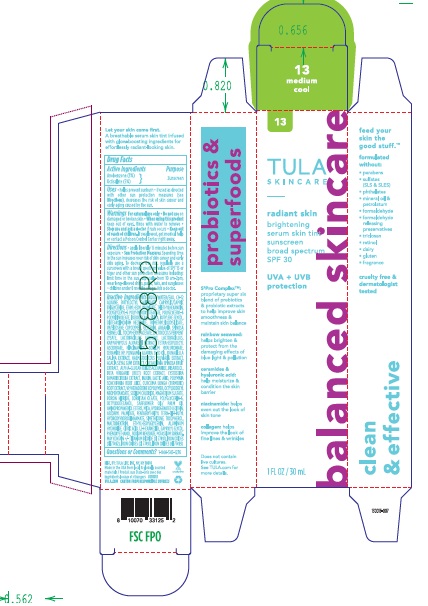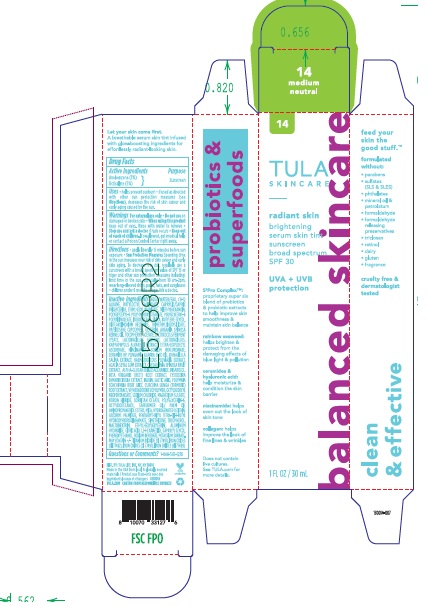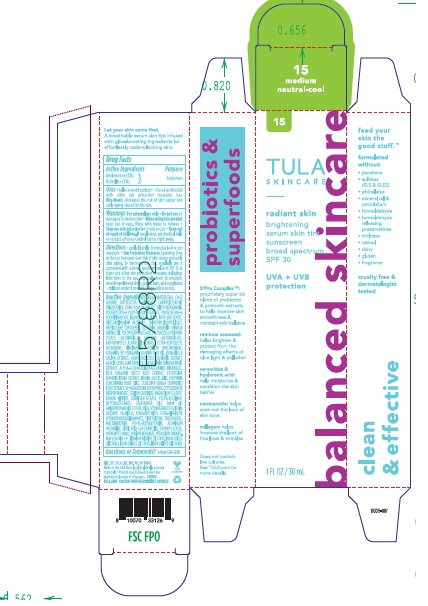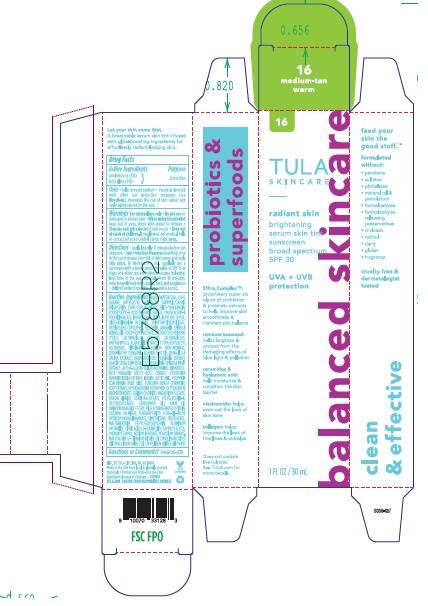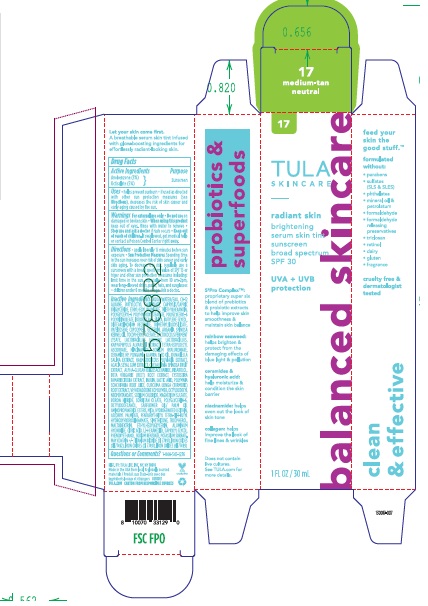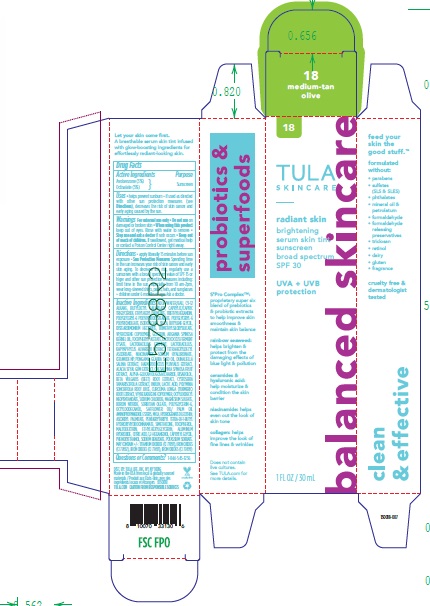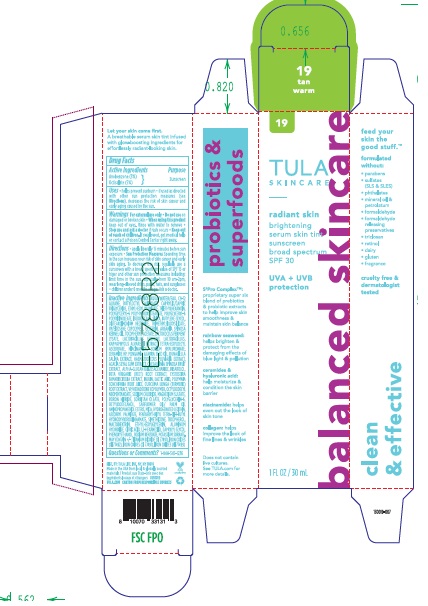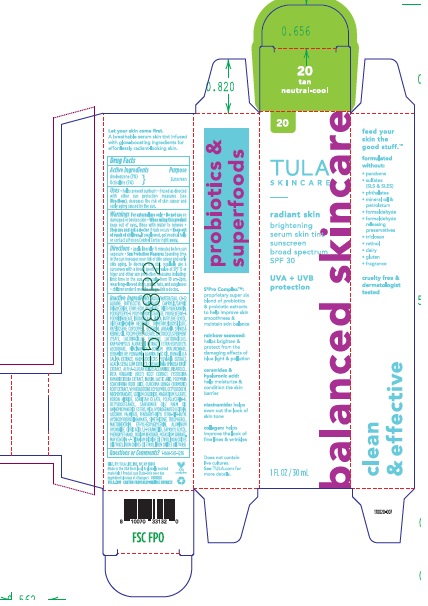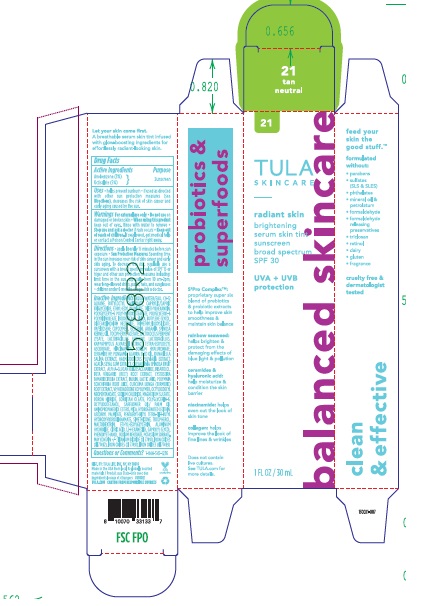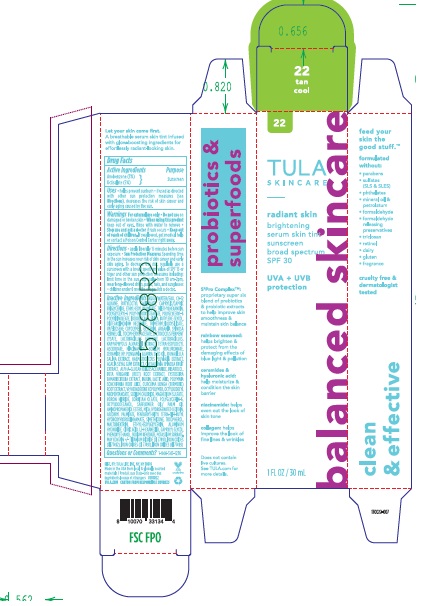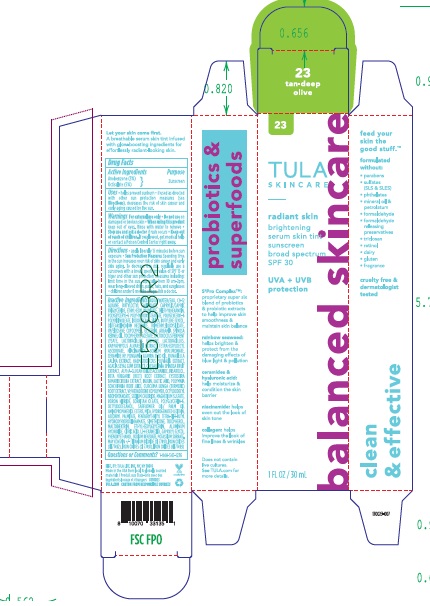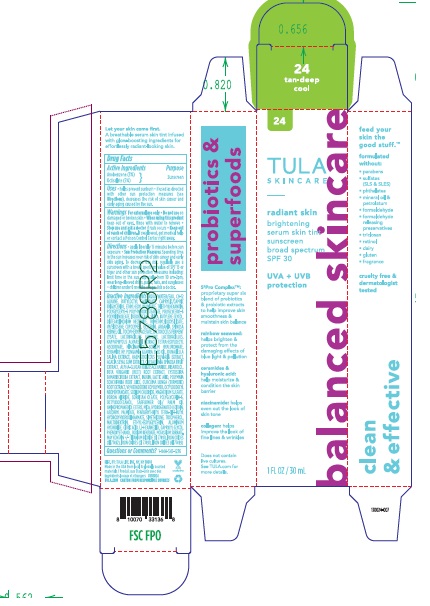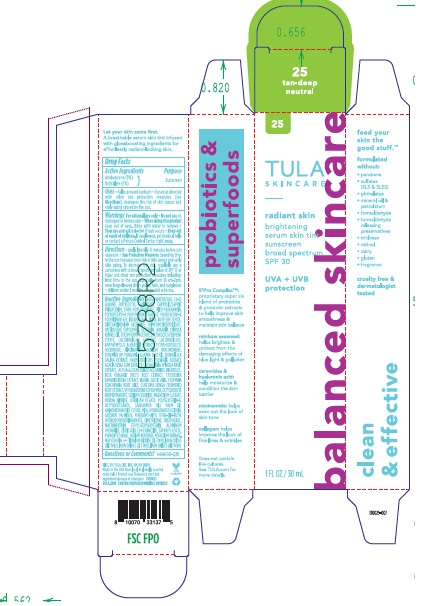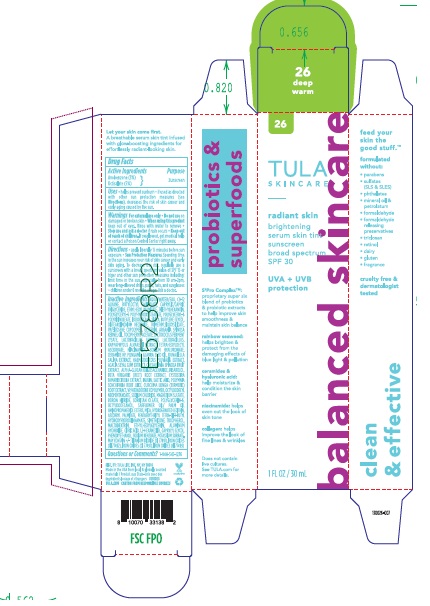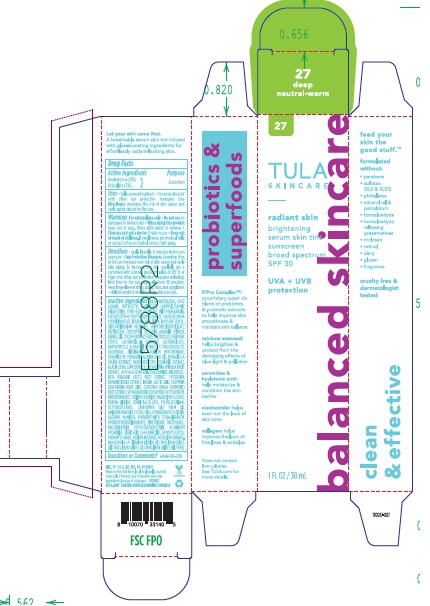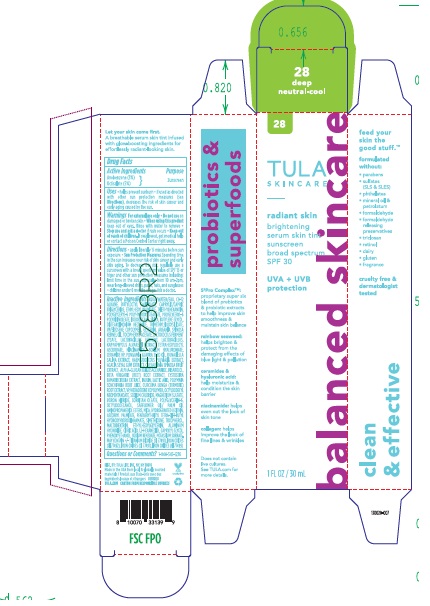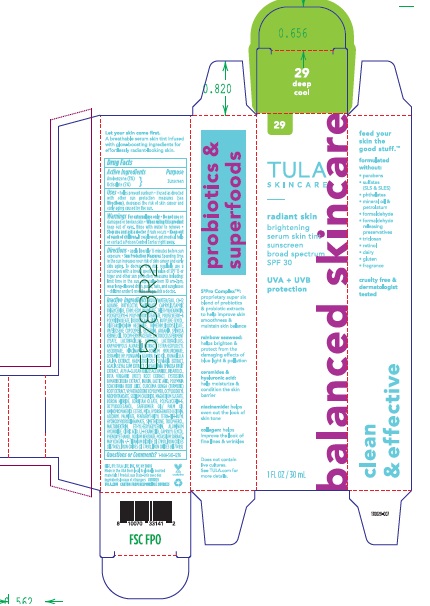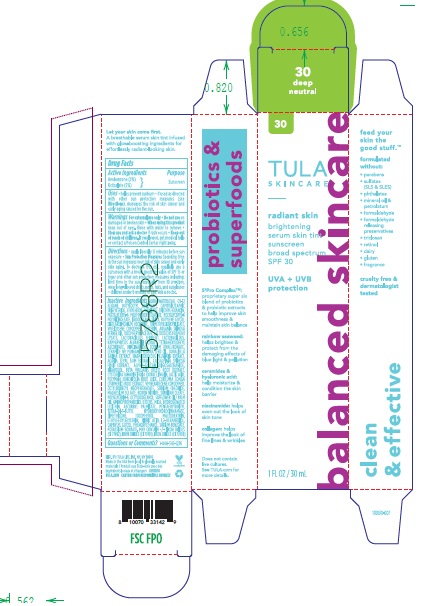 DRUG LABEL: Tula Skincare Radiant Skin Brightening Serum Skin Tint Broad Spectrum SPF 30
NDC: 84126-137 | Form: LIQUID
Manufacturer: The Procter & Gamble Manufacturing Company
Category: otc | Type: HUMAN OTC DRUG LABEL
Date: 20250603

ACTIVE INGREDIENTS: OCTISALATE 5 g/100 mL; AVOBENZONE 3 g/100 mL
INACTIVE INGREDIENTS: SMALLANTHUS SONCHIFOLIUS ROOT JUICE; TOCOPHEROL; MAGNESIUM SULFATE; DISTEARDIMONIUM HECTORITE; PONGAMIA GLABRA SEED OIL; POLYGLYCERIN-6; ASCORBYL PALMITATE; ALUMINUM HYDROXIDE; POTASSIUM SORBATE; WATER; TRIETHYLHEXANOIN; BEET; ETHYLHEXYL PALMITATE; CURCUMA LONGA (TURMERIC) ROOT; OCTYLDODECYL NEOPENTANOATE; TRIMETHYLSILOXYSILICATE (M/Q 0.6-0.8); SODIUM HYALURONATE; CERAMIDE NP; POLYGLYCERYL-6 POLYRICINOLEATE; ISODODECANE; ALPHA-TOCOPHEROL ACETATE; SILICA; BUTYLENE GLYCOL; SODIUM CHLORIDE; TITANIUM DIOXIDE; INULIN; BUTYLOCTYL SALICYLATE; LACTIC ACID; MICA; TETRAHEXYLDECYL ASCORBATE; DUNALIELLA SALINA; VP/HEXADECENE COPOLYMER; BORON NITRIDE; PENTAERYTHRITYL TETRA-DI-T-BUTYL HYDROXYHYDROCINNAMATE; CAPRYLYL GLYCOL; FERRIC OXIDE YELLOW; C9-12 ALKANE; CAPRYLIC/CAPRIC TRIGLYCERIDE; ARGANIA SPINOSA KERNEL OIL; SODIUM BENZOATE; FERRIC OXIDE RED; KAPPAPHYCUS ALVAREZII; NIACINAMIDE; SORBITAN OLEATE; MALTODEXTRIN; ETHYLHEXYLGLYCERIN; PHENOXYETHANOL; CITRIC ACID; HAEMATOCOCCUS PLUVIALIS; ALPHA-GLUCAN OLIGOSACCHARIDE; BISABOLOL; CYSTOSEIRA TAMARISCIFOLIA; OCTYLDODECANOL; 1,2-HEXANEDIOL; GLYCERIN; ACACIA SEYAL GUM; TARA SPINOSA FRUIT; FERROSOFERRIC OXIDE; HYDROGENATED SOYBEAN LECITHIN

Tula Skincare Radiant Skin Brightening Serum Skin Tint Broad Spectrum SPF 30 (by shades)

Drug Facts

ACTIVE INGREDIENT

AVOBENZONE 3%

OCTISALATE 5%

PURPOSE

Sunscreen

Uses

- helps prevent sunburn
- if used as directed with other sun protection measures (see Directions), decreases the risk of skin cancer and early skin aging caused by the sun

WARNINGS

For external use only

Do not use on damaged or broken skin

When using this product keep out of eyes. Rinse with water to remove.

Stop use and ask a doctor if rash occurs

Keep out of reach of children. If product is swallowed, get medical help or contact a Poison Control Center right away.

Directions

- apply liberally 15 minutes before sun exposure
- Sun Protection Measures. Spending time in the sun increases your risk of skin cancer and early skin aging. To decrease this risk, regularly use a sunscreen with a broad spectrum value of SPF 15 or higher and other sun protection measures including: limit time in sun, especially from 10 a.m. - 2 p.m, wear long-sleeved shirts, pants, hats, and sunglasses, children under 6 months: ask a doctor

Other information

- protect this product from excessive heat and direct sun

Inactive ingredients

Shades 1-28:
Water, C9-12 Alkane, Butyloctyl Salicylate, Caprylic/capric Triglyceride, Ethylhexyl Palmitate, Triethylhexanoin, Polyglyceryl-6 Polyhydroxystearate, Polyglyceryl-6 Polyricinoleate, Isododecane, Silica, Butylene Glycol, Disteardimonium Hectorite, Trimethylsiloxysilicate, Vp/eicosene Copolymer, Glycerin, Argania Spinosa Kernel Oil, Tocopheryl Acetate, Lactococcus Ferment Lysate, Lactobacillus Ferment, Lactobacillus, Kappaphycus Alvarezii Extract, Tetrahexyldecyl Ascorbate, Niacinamide, Sodium Hyaluronate, Ceramide Np, Pongamia Glabra Seed Oil, Dunaliella Salina Extract, Haematococcus Pluvialis Extract, Acacia Seyal Gum Extract, Caesalpinia Spinosa Fruit Extract, Alpha-glucan Oligosaccharide, Bisabolol, Beta Vulgaris (beet) Root Extract, Cystoseira Tamariscifolia Extract, Inulin, Lactic Acid, Polymnia Sonchifolia Root Juice, Curcuma Longa (turmeric) Root Extract, Vp/hexadecene Copolymer, Octyldodecyl Neopentanoate, Sodium Chloride, Magnesium Sulfate, Boron Nitride, Sorbitan Oleate, Polyglycerin-6, Octyldodecanol, Safflower Oil/ Palm Oil Aminopropanediol Esters, Mica, Hydrogenated Lecithin, Ascorbyl Palmitate, Pentaerythrityl Tetra-di-t-butyl Hydroxyhydrocinnamate, Simethicone, Tocopherol, Maltodextrin, Ethylhexylglycerin, Aluminum Hydroxide, Citric Acid, 1,2-hexanediol, Caprylyl Glycol, Phenoxyethanol, Sodium Benzoate, Potassium Sorbate

May Contain: Titanium Dioxide (ci 77891), Iron Oxides (ci 77492), Iron Oxides (ci 77491), Iron Oxides (ci 77499)

Shades 29- 30
Water, C9-12 Alkane, Butyloctyl Salicylate, Caprylic/capric Triglyceride, Ethylhexyl Palmitate, Triethylhexanoin, Polyglyceryl-6 Polyhydroxystearate, Polyglyceryl-6 Polyricinoleate, Isododecane, Silica, Butylene Glycol, Disteardimonium Hectorite, Trimethylsiloxysilicate, Vp/eicosene Copolymer, Glycerin, Argania Spinosa Kernel Oil, Tocopheryl Acetate, Lactococcus Ferment Lysate, Lactobacillus Ferment, Lactobacillus, Kappaphycus Alvarezii Extract, Tetrahexyldecyl Ascorbate, Niacinamide, Sodium Hyaluronate, Ceramide Np, Pongamia Glabra Seed Oil, Dunaliella Salina Extract, Haematococcus Pluvialis Extract, Acacia Seyal Gum Extract, Caesalpinia Spinosa Fruit Extract, Alpha-glucan Oligosaccharide, Bisabolol, Beta Vulgaris (beet) Root Extract, Cystoseira Tamariscifolia Extract, Inulin, Lactic Acid, Polymnia Sonchifolia Root Juice, Curcuma Longa (turmeric) Root Extract, Vp/hexadecene Copolymer, Octyldodecyl Neopentanoate, Sodium Chloride, Magnesium Sulfate, Boron Nitride, Sorbitan Oleate, Polyglycerin-6, Octyldodecanol, Safflower Oil/ Palm Oil Aminopropanediol Esters, Mica, Hydrogenated Lecithin, Ascorbyl Palmitate, Pentaerythrityl Tetra-di-t-butyl Hydroxyhydrocinnamate, Simethicone, Tocopherol, Maltodextrin, Ethylhexylglycerin, Citric Acid, 1,2-hexanediol, Caprylyl Glycol, Phenoxyethanol, Sodium Benzoate, Potassium Sorbate

May Contain: Iron Oxides (ci 77492), Iron Oxides (ci 77491), Iron Oxides (ci 77499)

Questions or comments?

Call 1-844-545-1236

Distr. by : TULA LIFE, INC. NY, NY 10016

PRINCIPAL DISPLAY PANEL - 30 mL CARTON

{Shade # and name}

TULA

SKINCARE

radiant skin

brightening

serum skin tint

sunscreen

broad spectrum

SPF 30

UVA + UVB

protection

30 mL (1 FL OZ)